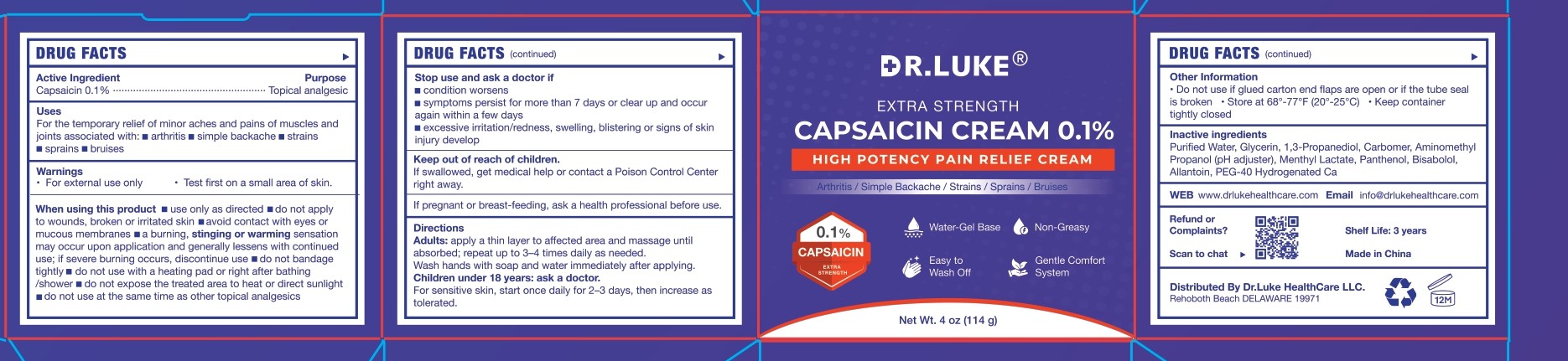 DRUG LABEL: Dr. Luke Capsaicin Cream
NDC: 87147-003 | Form: CREAM
Manufacturer: DANOUS LAND FLOOW LLC
Category: otc | Type: HUMAN OTC DRUG LABEL
Date: 20251001

ACTIVE INGREDIENTS: CAPSAICIN 0.1 g/100 g
INACTIVE INGREDIENTS: CARBOMER; ALLANTOIN; PEG-40 HYDROGENATED CASTOR OIL; PANTHENOL; WATER; BISABOLOL; PHENOXYETHANOL; GLYCERIN; ETHYLHEXYLGLYCERIN; MENTHYL LACTATE; AMINOMETHYL PROPANOL

ACTIVE INGREDIENT

Capsaicin 0.1% w/w – External Analgesic

WHEN USING

■ use only as directed ■ do not apply to wounds, broken or irritated skin ■ avoid contact with eyes or mucous membranes ■ a burning, stinging or warming sensation may occur upon application and generally lessens with continued use; if severe burning occurs, discontinue use ■ do not bandage tightly ■ do not use with a heating pad or right after bathing/shower ■ do not expose the treated area to heat or direct sunlight ■ do not use at the same time as other topical analgesics

DO NOT USE

■ condition worsens ■ symptoms persist for more than 7 days or clear up and occur again within a few days ■ excessive irritation/redness, swelling, blistering or signs of skin injury develop

KEEP OUT OF REACH OF CHILDREN

If swallowed, get medical help or contact a Poison Control Center right away.

PREGNANCY OR BREAST FEEDING

ask a health professional before use.

WARNINGS

For external use only
Test first on a small area of skin.

INACTIVE INGREDIENT

Purified Water, Glycerin, 1,3-Propanediol, Carbomer, Aminomethyl Propanol (pH adjuster), Menthyl Lactate, Panthenol, Bisabolol, Allantoin, PEG-40 Hydrogenated Castor Oil, Phenoxyethanol, Ethylhexylglycerin.

INSTRUCTIONS FOR USE

Adults:

apply a thin layer to affected area and massage until absorbed; repeat up to 3–4 times daily as needed.
Wash hands with soap and water immediately after applying.

Children under 18 years:

ask a doctor.

For sensitive skin, start once daily for 2–3 days, then increase as tolerated.

INDICATIONS AND USAGE

For the temporary relief of minor aches and pains of muscles and joints associated with: ■ arthritis ■ simple backache ■ strains ■ sprains ■ bruises

DOSAGE AND ADMINISTRATION

Apply to affected area not more than 3–4 times daily.

PURPOSE

Topical analgesic